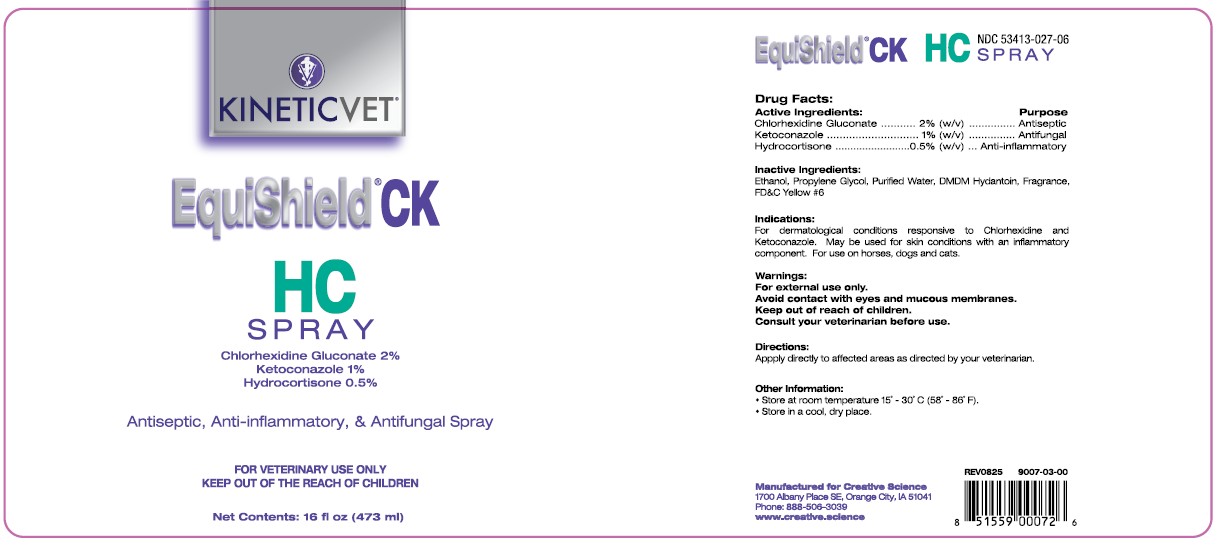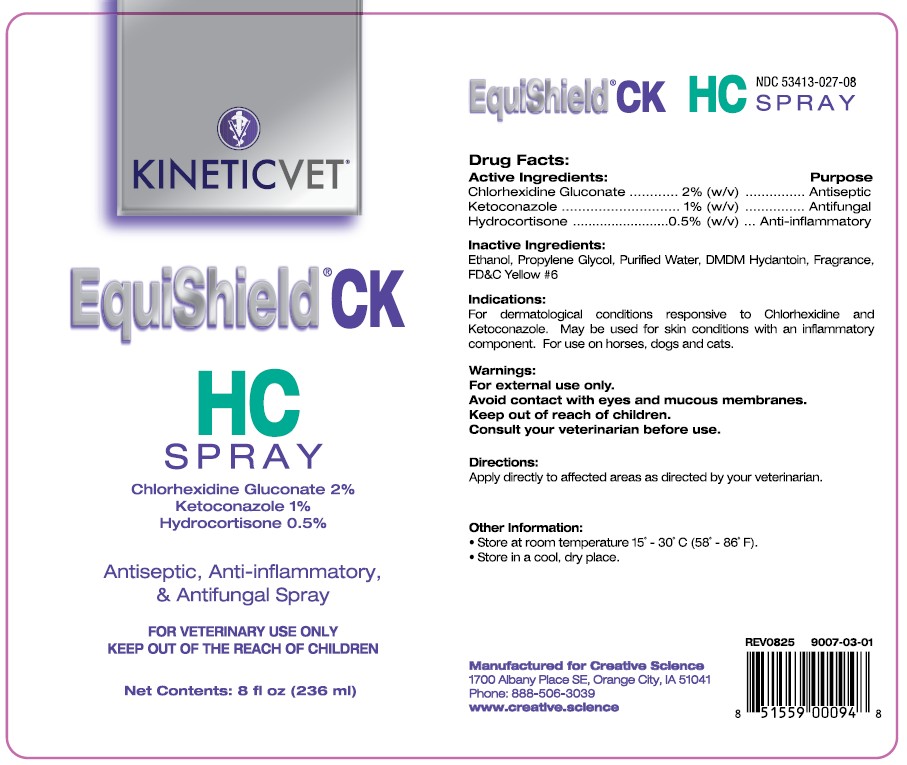 DRUG LABEL: EquiShield CK HC
NDC: 53413-027 | Form: SPRAY
Manufacturer: Creative Science
Category: animal | Type: OTC ANIMAL DRUG LABEL
Date: 20251217

ACTIVE INGREDIENTS: CHLORHEXIDINE GLUCONATE 20 mg/1 mL; HYDROCORTISONE 10 mg/1 mL

EquiShield CK HC SPRAY

NDC 53413-027-06 - 16 oz NDC 53413-027-08 - 8 oz Drug Facts:

Active Ingredients:

Chlorhexidine Gluconate ........... 2% (w/v)
Ketoconazole ........................... 1% (w/v)
Hydrocortisone ...................... 0.5% (w/v)

Purpose:

Antiseptic

Antifungal

Anti-Inflammatory

Inactive Ingredients:

Ethanol, Propylene Glycol, Purified Water, DMDM Hydantoin, Fragrance, FD&C Yellow #6

Indications:

For dermatological conditions responsive to Chlorhexidine and Ketoconazole. May be used for skin conditions with an inflammatory component. For use on horses, dogs and cats.

Warnings:

For external use only.
Avoid contact with eyes and mucous membranes.
Consult your veterinarian before use.

Keep out of reach of children.

Directions:

Apply directly to affected areas as directed by your veterinarian.

Other Information:

• Store at room temperature 15˚ - 30˚C (58˚ - 86˚F).
• Store in a cool, dry place.

REV0825 9007-03-00 UPC 851559000726 16 oz

REV0825 9007-03-01 UPC 851559000948 8 oz

Manufactured for Creative Science

1700 Albany Place SE, Orange City, IA 51041

Phone: 888-506-3039

www.creative.science

PACKAGE LABEL

EquiShield® CK HC SPRAY

Chlorhexidine Gluconate 2%

Ketoconazole 1%

Hydrocortisone 0.5%

Antisptic & Anti-inflammatory & Antifungal Spray

FOR VETERINARY USE ONLY

KEEP OUT OF THE REACH OF CHILDREN

Net Contents: 8 fl oz (236 ml)

Net Contents: 16 fl oz (473 ml)